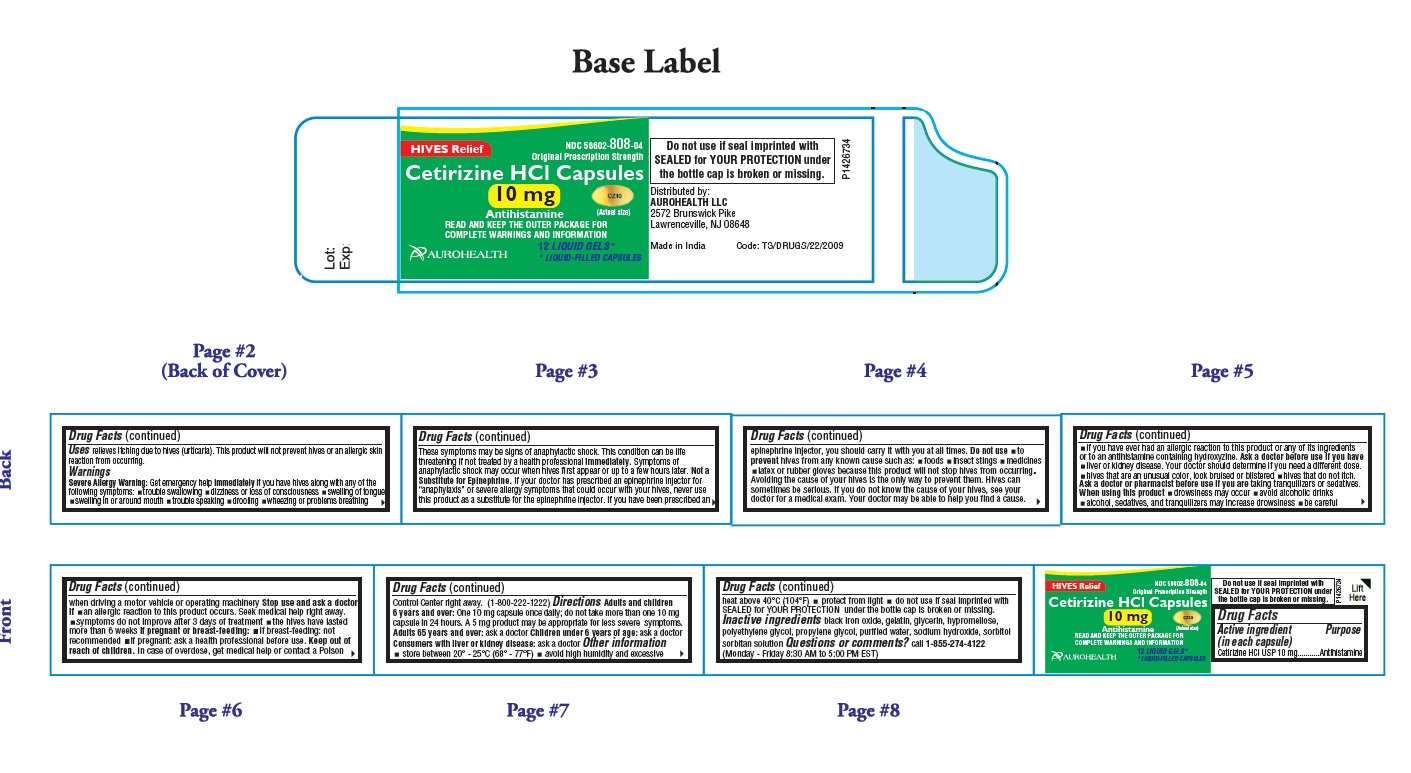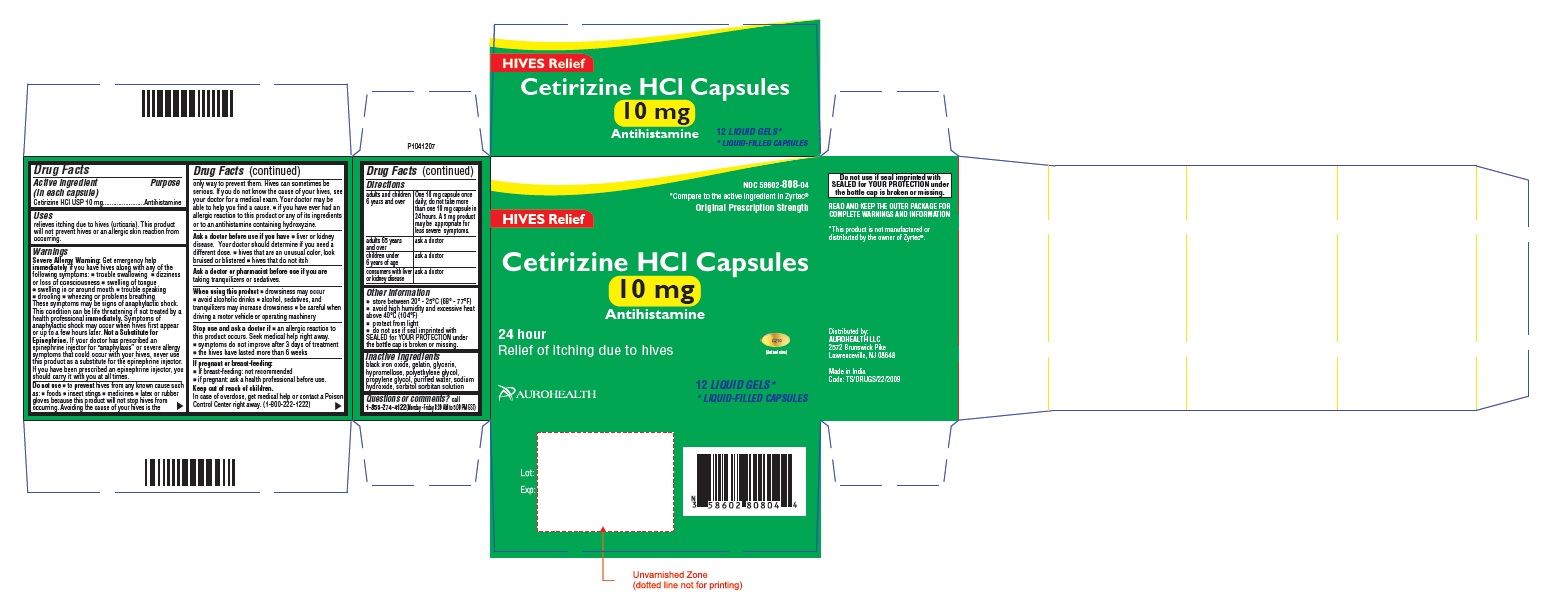 DRUG LABEL: Cetirizine Hydrochloride (Hives Relief)
NDC: 58602-808 | Form: CAPSULE
Manufacturer: Aurohealth LLC
Category: otc | Type: Human OTC Drug Label
Date: 20200914

ACTIVE INGREDIENTS: CETIRIZINE HYDROCHLORIDE 10 mg/1 1
INACTIVE INGREDIENTS: FERROSOFERRIC OXIDE; GELATIN, UNSPECIFIED; GLYCERIN; HYPROMELLOSE 2910 (6 MPA.S); POLYETHYLENE GLYCOL 400; PROPYLENE GLYCOL; WATER; SODIUM HYDROXIDE; SORBITOL

Cetirizine HCl Capsules 10 mg (Hives Relief)
Drug Facts

Active ingredient (in each capsule)

Cetirizine HCI USP 10 mg

Purpose

Antihistamine

Uses

relieves itching due to hives (urticaria). This product will not prevent hives or an allergic skin reaction from occuring.

Warnings

Severe Allergy Warning: Get emergency help immediately if you have hives along with any of the following symptoms:

- trouble swallowing
- dizziness or loss of consciousness
- swelling of tongue
- swelling in or around mouth
- trouble speaking
- drooling
- wheezing or problems breathing

These symptoms may be signs of anaphylactic shock. This condition can be life threatening if not treated by a health professional immediately. Symptoms of anaphylactic shock may occur when hives first appear or up to a few hours later.
Not a Substitute for Epinephrine. If your doctor has prescribed an epinephrine injector for "anaphylaxis" or severe allergy symptoms that could occur with your hives, never use this product as a substitute for the epinephrine injector. If you have been prescribed an epinephrine injector, you should carry it with you at all times.

Do not use

- to prevent hives from any known cause such as:
  - foods
  - insect stings
  - medicines
  - latex or rubber gloves

because this product will not stop hives from occuring. Avoiding the cause of your hives is the only way to prevent them. Hives can sometimes be serious. If you do not know the cause of your hives, see your doctor for a medical exam. Your doctor may be able to help you find a cause.

- if you have ever had an allergic reaction to this product or any of its ingredients or to an antihistamine containing hydroxyzine.

Ask a doctor before use if you have

- liver or kidney disease. Your doctor should determine if you need a different dose.
- hives that are an unusual color, look bruised or blistered
- hives that do not itch

Ask a doctor or pharmacist before use if you are taking tranquilizers or sedatives.

When using this product

- drowsiness may occur
- avoid alcoholic drinks
- alcohol, sedatives, and tranquilizers may increase drowsiness
- be careful when driving a motor vehicle or operating machinery

Stop use and ask a doctor if

- an allergic reaction to this product occurs. Seek medical help right away.
- symptoms do not improve after 3 days of treatment.
- the hives have lasted more than 6 weeks.

If pregnant or breast-feeding:

- If breast-feeding: not recommended
- if pregnant: ask a health professional before use.

Keep out of reach of children.

In case of overdose, get medical help or contact a Poison Control Center right away. [1-800-222-1222]

Directions

adults and children 6 years and over | one 10 mg capsule once daily; do not take more than one 10 mg capsule in 24 hours. A 5 mg product may be appropriate for less severe symptoms.
adults 65 years and over | ask a doctor
children under 6 years of age | ask a doctor
consumers with liver or kidney disease | ask a doctor

Other information

- store between 20° - 25°C (68° - 77°F)
- avoid high humidity and excessive heat above 40°C (104°F)
- protect from light
- do not use if seal imprinted with SEALED for YOUR PROTECTION under the bottle cap is broken or missing.

Inactive ingredients

black iron oxide, gelatin, glycerin, hypromellose, polyethylene glycol, propylene glycol, purified water, sodium hydroxide, sorbitol sorbitan solution

Questions or comments?

call 1-855-274-4122 (Monday - Friday 8:30 AM to 5:00 PM EST)

Distributed by:
AUROHEALTH LLC
2572 Brunswick Pike
Lawrenceville, NJ 08648
Made in India
Code: TS/DRUGS/22/2009

PACKAGE LABEL-PRINCIPAL DISPLAY PANEL - 10 mg (12's Capsule Container Label)

HIVES Relief NDC 58602-808-04
Original Prescription Strength
Cetirizine HCl Capsules
10 mg CZ10
Antihistamine (Actual Size)
READ AND KEEP THE OUTER PACKAGE FOR
COMPLETE WARNINGS AND INFORMATION
12 LIQUID GELS*
* LIQUID-FILLED CAPSULES
AUROHEALTH

PACKAGE LABEL-PRINCIPAL DISPLAY PANEL - 10 mg (12's Capsule Container Carton Label)

NDC 58602-808-04
*Compare to the active ingredient in Zyrtec®
Original Prescription Strength
HIVES Relief
Cetirizine HCl Capsules
10 mg
Antihistamine
24 hour CZ10
Relief of itching due to hives (Actual Size)
12 LIQUID GELS*
* LIQUID-FILLED CAPSULES
AUROHEALTH